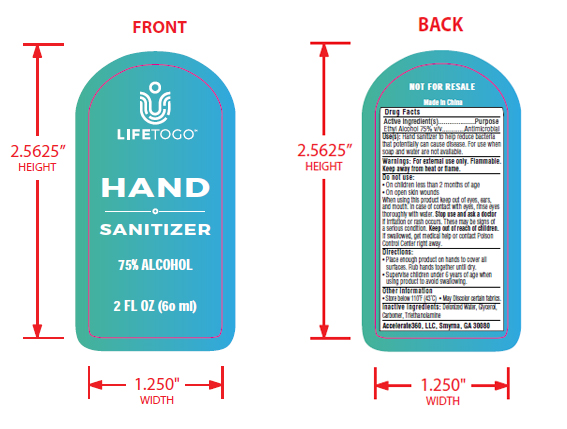 DRUG LABEL: 75% alcohol hand sanitzer
NDC: 74212-1001 | Form: GEL
Manufacturer: Accelerate360 Llc
Category: otc | Type: HUMAN OTC DRUG LABEL
Date: 20200810

ACTIVE INGREDIENTS: ALCOHOL 75 mL/100 mL
INACTIVE INGREDIENTS: WATER; CARBOMER HOMOPOLYMER, UNSPECIFIED TYPE; TROLAMINE; GLYCERIN

75% alcohol hand sanitzer

Active ingredient(s)

Ethyl Alcohol 75% v/v.............Antimicrobial

PURPOSE

Hand sanitizer, Antimicrobial

Uses

Hand sanitizer to help reduce bacteria that potentially can cause disease. For use when soap and water are not available.

Warnings

For external use only. Flammable. Keep away from heat or flame.

Do not use

• On children less than 2 months of age
• On open skin wounds.

When using this product keep out of eyes, ears, and mouth. In case of contact with eyes, rinse eyes thoroughly with water.

Stop use and ask a doctor if irritation or rash occurs. These may be signs of a serious condition.

Keep out of reach of children. If swallowed, get medical help or contact Poison Control Center right away.

Directions

Place enough product on hands to cover all surfaces. Rub hands together until dry.
Supervise children under 6 years of age when using product to avoid swallowing.

Other information

• Store below 110°F (43°C)

• May Discolor certain fabrics.

Inactive ingredients

Deionized Water, Glycerol, Carbomer, Triethanolamine

Accelerate360, LLC, Smyrna, GA 30080

PACKAGE LABEL

60ml 74212-1001-1

LIFETOGO

HAND

SANITIZER

75% ALCOHOL

2 FL OZ (60 ml)